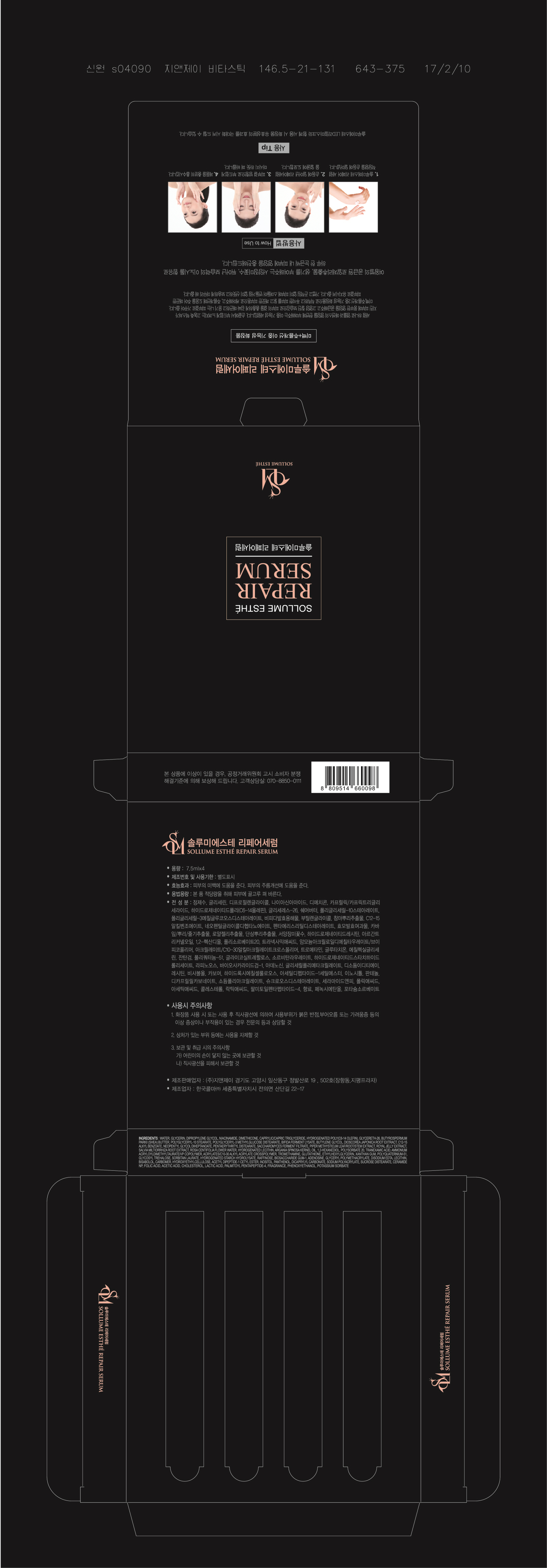 DRUG LABEL: SOLLUME ESTHE REPAIR SERUM
NDC: 71551-0001 | Form: GEL
Manufacturer: G&J Co., Ltd.
Category: otc | Type: HUMAN OTC DRUG LABEL
Date: 20170627

ACTIVE INGREDIENTS: ADENOSINE 0.04 g/100 mL; NIACINAMIDE 5 g/100 mL
INACTIVE INGREDIENTS: WATER; GLYCERIN

Drug Facts

ACTIVE INGREDIENT

niacinamide, adenosine

INACTIVE INGREDIENT

WATER, GLYCERIN, DIPROPYLENE GLYCOL, DIMETHICONE, CAPRYLIC/CAPRIC TRIGLYCERIDE, HYDROGENATED POLY(C6-14 OLEFIN), GLYCERETH-26, BUTYROSPERMUM PARKII (SHEA) BUTTER, POLYGLYCERYL-10 STEARATE, POLYGLYCERYL-3 METHYLGLUCOSE DISTEARATE, BIFIDA FERMENT LYSATE, BUTYLENE GLYCOL, DIOSCOREA JAPONICA ROOT EXTRACT, C12-15 ALKYL BENZOATE, NEOPENTYL GLYCOL DIHEPTANOATE, PENTAERYTHRITYL DISTEARATE, SACCHAROMYCES FERMENT FILTRATE, PIPER METHYSTICUM LEAF/ROOT/STEM EXTRACT, ROYAL JELLY EXTRACT, SALVIA MILTIORRHIZA ROOT EXTRACT, ROSA CENTIFOLIA FLOWER WATER, HYDROGENATED LECITHIN, ARGANIA SPINOSA KERNEL OIL, 1,2-HEXANEDIOL, POLYSORBATE 20, TRANEXAMIC ACID, AMMONIUM ACRYLOYLDIMETHYLTAURATE/VP COPOLYMER, ACRYLATES/C10-30 ALKYL ACRYLATE CROSSPOLYMER, TROMETHAMINE, GLUTATHIONE, ETHYLHEXYLGLYCERIN, XANTHAN GUM, POLYQUATERNIUM-51, GLYCOSYL TREHALOSE, SORBITAN LAURATE, HYDROGENATED STARCH HYDROLYSATE, RAFFINOSE, BIOSACCHARIDE GUM-1, GLYCERYL POLYMETHACRYLATE, DISODIUM EDTA, LECITHIN, BISABOLOL, CARBOMER, HYDROXYETHYLCELLULOSE, ACETYL DIPEPTIDE-1 CETYL ESTER, INOSITOL, PANTHENOL, DICAPRYLYL CARBONATE, SODIUM POLYACRYLATE, SUCROSE DISTEARATE, CERAMIDE NP, FOLIC ACID, ACETIC ACID, CHOLESTEROL, LACTIC ACID, PALMITOYL PENTAPEPTIDE-4, FRAGRANCE, PHENOXYETHANOL, POTASSIUM SORBATE

PURPOSE

Whitening + wrinkle dual functional cosmetics - It helps Whitening your skin. it Helps improve wrinkles in the skin.

keep out of reach of the children

INDICATIONS AND USAGE

1.Take out appropriate amount of this serum on the hand
2.spread it evenly on the skin.
3.Massage gently in the skin.
4.fully absorbs the product.

WARNINGS

•Precautions when using

1. After using or using cosmetics, consult a specialist if you have any abnormal symptoms such as red spots, swelling or itching or side effects caused by direct sunlight.

2. Do not use on wounded area

3. storage and handling Precautions

a) Keep out of the reach of children

b) Store away from direct sunlight.

DOSAGE AND ADMINISTRATION

for external use only